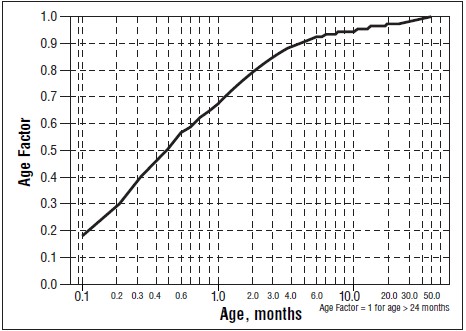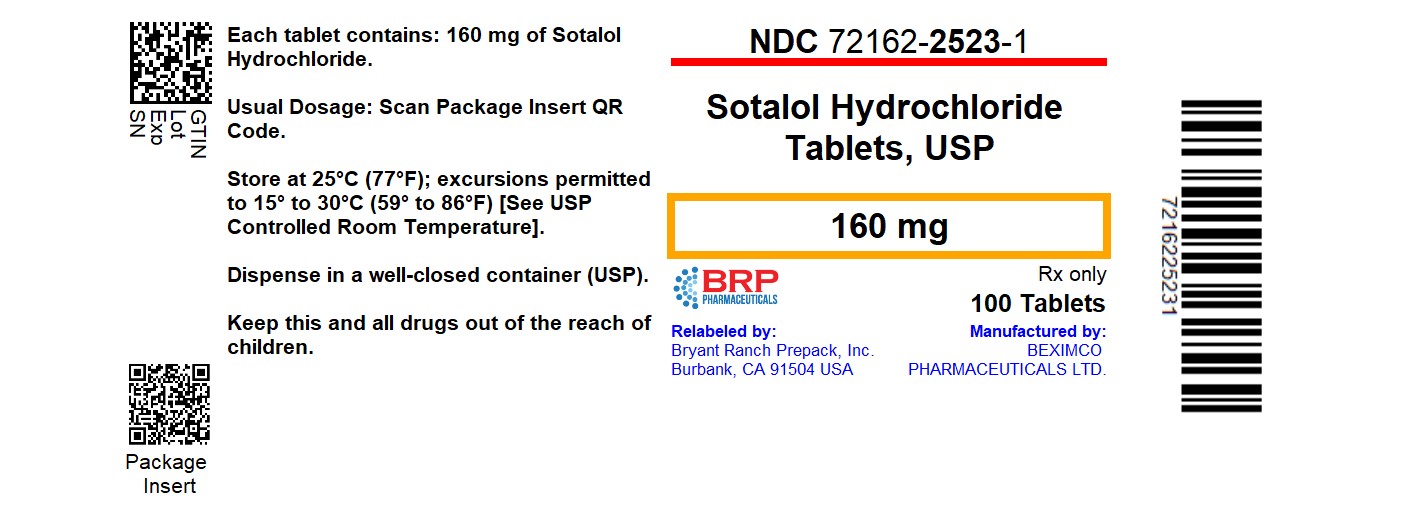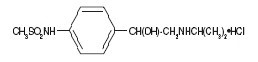 DRUG LABEL: Sotalol
NDC: 72162-2523 | Form: TABLET
Manufacturer: Bryant Ranch Prepack
Category: prescription | Type: HUMAN PRESCRIPTION DRUG LABEL
Date: 20250711

ACTIVE INGREDIENTS: SOTALOL HYDROCHLORIDE 160 mg/1 1
INACTIVE INGREDIENTS: LACTOSE MONOHYDRATE; MICROCRYSTALLINE CELLULOSE; STARCH, CORN; FD&C BLUE NO. 2; SILICON DIOXIDE; STEARIC ACID; MAGNESIUM STEARATE

HIGHLIGHTS OF PRESCRIBING INFORMATION

These highlights do not include all the information needed to use SOTALOL HYDROCHLORIDE TABLETS safely and effectively. See full prescribing information for SOTALOL HYDROCHLORIDE TABLETS.SOTALOL HYDROCHLORIDE tablets, for oral use
Initial U.S. Approval: 1992

WARNING: LIFE THREATENING PROARRHYTHMIA
See full prescribing information for complete boxed warning.

- Sotalol Hydrochloride Tablets can cause life threatening ventricular tachycardia associated with QT interval prolongation.
- If the QT interval prolongs to 500 msec or greater, reduce the dose, lengthen the dosing interval, or discontinue the drug.
- Initiate or reinitiate in a facility that can provide cardiac resuscitation and continuous electrocardiographic monitoring.
- Adjust the dosing interval based on creatinine clearance.

1. INDICATIONS AND USAGE

Sotalol Hydrochloride Tablets are an antiarrhythmic indicated for:

- the treatment of life threatening ventricular arrhythmias (1.1)

Limitations of Use

- Avoid use in patients with asymptomatic ventricular premature contraction (1.1)

2 DOSAGE AND ADMINISTRATION

- Sotalol Hydrochloride Tablets: Initial dosage in adults is 80 mg twice daily. Increase the dose as needed in increments of 80 mg/day, every 3 days to a maximum 320 mg total daily dose (2.2)
- Pediatrics: Dosage depends on age (2.4)

3 DOSAGE FORMS AND STRENGTHS

80 mg,120 mg and 160 mg tablets (3)

4 CONTRAINDICATIONS

For the treatment of ventricular arrythmias

- Sinus bradycardia, 2nd or 3rd degree AV block, sick sinus syndrome (4)
- Congenital or acquired long QT syndrome, (4)
- Serum potassium <4 mEq/L(4)
- Cardiogenic shock, decompensated heart failure (4)
- Bronchial asthma or related bronchospastic conditions (4)
- Hypersensitivity to sotalol (4)

5 WARNINGS AND PRECAUTIONS

- QT prolongation, bradycardia, AV block, hypotension, worsening heart failure: Reduce dose or discontinue (5.1)
- Acute exacerbation of coronary artery disease upon cessation of therapy: Do not abruptly discontinue (5.5)
- Correct any electrolyte disturbances (5.1)
- May mask symptoms of hypoglycemia or worsen hyperglycemia in diabetic patients; monitor (5.7)

6 ADVERSE REACTIONS

The most common adverse reactions (≥2%) for Sotalol Hydrochloride Tablets are: fatigue 4%, bradycardia (less than 50 bpm) 3%, dyspnea 3%, proarrhythmia 3%, asthenia 2%, and dizziness 2%. (6)

To report SUSPECTED ADVERSE REACTIONS, contact Beximco Pharmaceuticals USA Inc. at 877-372-6093 or FDA at 1-800-FDA-1088 or www.fda.gov/medwatch.

7 DRUG INTERACTIONS

Class I or III Antiarrhythmics or other drugs that prolong the QT interval: Avoid concomitant use (7.1)
Digoxin, calcium channel blocker: increased risk of bradycardia, hypotension, heart failure (7.2)
Dosage of insulin or antidiabetic drugs may need adjustment (7.5)
Aluminum or magnesium-based antacids reduce sotalol exposure (7.7)

FULL PRESCRIBING INFORMATION

WARNING: LIFE THREATENING PROARRHYTHMIA
To minimize the risk of drug-induced arrhythmia, initiate or reinitiate oral sotalol in a facility that can provide cardiac resuscitation and continuous electrocardiographic monitoring.

Sotalol can cause life threatening ventricular tachycardia associated with QT interval prolongation.

If the QT interval prolongs to 500 msec or greater, reduce the dose, lengthen the dosing interval, or discontinue the drug.

Calculate creatinine clearance to determine appropriate dosing [see Dosage and Administration (2.5)].

1. INDICATIONS AND USAGE

1.1 Life-Threatening Ventricular Arrhythmias

Sotalol Hydrochloride Tablets are indicated for the treatment of life-threatening, documented ventricular arrhythmias, such as sustained ventricular tachycardia (VT).

Limitation of Use:

Sotalol Hydrochloride Tablets may not enhance survival in patients with ventricular arrhythmias. Because of the proarrhythmic effects of Sotalol Hydrochloride Tablets, including a 1.5 to 2% rate of Torsade de Pointes (TdP) or new ventricular tachycardia/fibrillation (VT/VF) in patients with either non-sustained ventricular tachycardia (NSVT) or supraventricular arrhythmias (SVT), its use in patients with less severe arrhythmias, even if the patients are symptomatic, is generally not recommended. Avoid treatment of patients with asymptomatic ventricular premature contractions [ see Warnings and Precautions (5.2) .]

2 DOSAGE AND ADMINISTRATION

2.1 General Safety Measures for Initiation of Oral Sotalol Therapy

Withdraw other antiarrhythmic therapy before starting Sotalol Hydrochloride Tablets and monitor carefully for a minimum of 2 to 3 plasma half-lives if the patient's clinical condition permits [see Drug Interactions (7)].

Hospitalize patients initiated or re-initiated on sotalol for at least 3 days or until steady-state drug levels are achieved, in a facility that can provide cardiac resuscitation and continuous electrocardiographic monitoring. Initiate oral sotalol therapy in the presence of personnel trained in the management of serious arrhythmias. Perform a baseline ECG to determine the QT interval and measure and normalize serum potassium and magnesium levels before initiating therapy. Measure serum creatinine and calculate an estimated creatinine clearance in order to establish the appropriate dosing interval (insert cross ref to renal dosing). Continually monitor patients with each uptitration in dose, until they reach steady state. Determine QTc 2 to 4 hours after every dose.

Discharge patients on sotalol therapy from an in-patient setting with an adequate supply of sotalol to allow uninterrupted therapy until the patient can fill a sotalol prescription.

Advise patients who miss a dose to take the next dose at the usual time. Do not double the dose or shorten the dosing interval.

2.2 Adult Dose for Ventricular Arrhythmias

The recommended initial dose is 80 mg twice daily. This dose may be increased in increments of 80 mg per day every 3 days provided the QTc <500 msec [see Warnings and Precautions (5.1)]. Continually monitor patients until steady state blood levels are achieved. In most patients, a therapeutic response is obtained at a total daily dose of 160 to 320 mg/day, given in two or three divided doses (because of the long terminal elimination half- life of sotalol, dosing more than a two times a day is usually not necessary). Oral doses as high as 480-640 mg/day have been utilized in patients with refractory life-threatening arrhythmias.

2.4 Pediatric Dose for Ventricular Arrhythmias

Use the same precautionary measures for children as you would use for adults when initiating and re-initiating sotalol treatment.

For children aged about 2 years and older

For children aged about 2 years and older, with normal renal function, doses normalized for body surface area are appropriate for both initial and incremental dosing. Since the Class III potency in children is not very different from that in adults, reaching plasma concentrations that occur within the adult dose range is an appropriate guide [see Clinical Pharmacology (12.1, 12.3)].

From pediatric pharmacokinetic data the following is recommended:

For initiation of treatment, 30 mg/m^2 three times a day (90 mg/m2 total daily dose) is approximately equivalent to the initial 160 mg total daily dose for adults. Subsequent titration to a maximum of 60 mg/m^2 (approximately equivalent to the 360 mg total daily dose for adults) can then occur. Titration should be guided by clinical response, heart rate and QTc, with increased dosing being preferably carried out in-hospital. At least 36 hours should be allowed between dose increments to attain steady-state plasma concentrations of sotalol in patients with age-adjusted normal renal function.

For children aged about 2 years or younger

For children aged about 2 years or younger, the above pediatric dosage should be reduced by a factor that depends heavily upon age, as shown in the following graph, age plotted on a logarithmic scale in months.

For a child aged 20 months, the dosing suggested for children with normal renal function aged 2 years or greater should be multiplied by about 0.97; the initial starting dose would be (30 X 0.97)=29.1 mg/m^2, administered three times daily. For a child aged 1 month, the starting dose should be multiplied by 0.68; the initial starting dose would be (30 X 0.68)=20 mg/m^2, administered three times daily. For a child aged about 1 week, the initial starting dose should be multiplied by 0.3; the starting dose would be (30 X 0.3)=9 mg/m^2. Use similar calculations for dose titration.

Since the half-life of sotalol decreases with decreasing age (below about 2 years), time to steady-state will also increase. Thus, in neonates the time to steady-state may be as long as a week or longer.

2.5 Dosage for Patients with Renal Impairment

Adults

Use of sotalol in any age group with decreased renal function should be at lower doses or increased intervals between doses. It will take much longer to reach steady-state with any dose and/or frequency of administration. Closely monitor heart rate and QTc.

Dose escalations in renal impairment should be done after administration of at least 5 doses at appropriate intervals (Table 1). Sotalol is partly removed by dialysis; specific advice is unavailable on dosing patients on dialysis.

The initial dose of 80 mg and subsequent doses should be administered at the intervals listed in Table 1.

Table 1: Dosing Intervals for treatment of Ventricular Arrhythmias in renal impairment
Creatinine Clearance mL/min | Dosing Interval (hours)
> 60 | 12
30–59 | 24
10–29 | 36–48
< 10 | Dose should be individualized

2.6 Preparation of Extemporaneous Oral Solution

Sotalol Hydrochloride Syrup 5 mg/mL can be compounded using Simple Syrup containing 0.1% sodium benzoate (Syrup, NF) as follows:

1. Measure 120 mL of Simple Syrup.
2. Transfer the syrup to a 6-ounce amber plastic (polyethylene terephthalate [PET]) prescription bottle. An oversized bottle is used to allow for a headspace, so that there will be more effective mixing during shaking of the bottle.
3. Add five (5) Sotalol Hydrochloride 120 mg tablets to the bottle. These tablets are added intact; it is not necessary to crush the tablets. The addition of the tablets can also be done first. The tablets can also be crushed if preferred. If the tablets are crushed, care should be taken to transfer the entire quantity of tablet powder into the bottle containing the syrup.
4. Shake the bottle to wet the entire surface of the tablets. If the tablets have been crushed, shake the bottle until the endpoint is achieved.
5. Allow the tablets to hydrate for at least two hours.
6. After at least two hours have elapsed, shake the bottle intermittently over the course of at least another two hours until the tablets are completely disintegrated. The tablets can be allowed to hydrate overnight to simplify the disintegration process.

The endpoint is achieved when a dispersion of fine particles in the syrup is obtained.

This compounding procedure results in a solution containing 5 mg/mL of sotalol HCl. The fine solid particles are the water-insoluble inactive ingredients of the tablets.

Stability studies indicate that the suspension is stable for three months when stored at 15°C to 30°C (59°F to 86°F) [see USP Controlled Room Temperature] and ambient humidity.

3 DOSAGE FORMS AND STRENGTHS

Sotalol Hydrochloride Tablets are supplied as capsule-shaped, light-blue, scored tablets:

- 80 mg imprinted with “B104” on one side and 80 mg on the other
- 120 mg imprinted with “B105” on one side and 120 mg on the other
- 60 mg imprinted with “B105” on one side and 160 mg on the other

4 CONTRAINDICATIONS

Sotalol Hydrochloride Tablets are contraindicated in patients with:

- Sinus bradycardia, sick sinus syndrome, second and third degree AV block, unless a functioning pacemaker is present
- Congenital or acquired long QT syndromes
- Cardiogenic shock or decompensated heart failure
- Serum potassium <4 mEq/L
- Bronchial asthma or related bronchospastic conditions
- Hypersensitivity to sotalol

5 WARNINGS AND PRECAUTIONS

5.1 QT Prolongation and Proarrhythmia

Sotalol Hydrochloride Tablets can cause serious and potentially fatal ventricular arrhythmias such as sustained VT/VF, primarily Torsade de Pointes (TdP) type ventricular tachycardia, a polymorphic ventricular tachycardia associated with QT interval prolongation. Factors such as reduced creatinine clearance, female sex, higher doses, reduced heart rate and history of sustained VT/VF or heart failure increase the risk of TdP. The risk of TdP can be reduced by adjustment of the sotalol dose according to creatinine clearance and by monitoring the ECG for excessive increases in the QT interval [ see Dosage and Administration (2.1) ].

Correct hypokalemia or hypomagnesemia prior to initiating Sotalol Hydrochloride Tablets, as these conditions can exaggerate the degree of QT prolongation, and increase the potential for Torsade de Pointes. Special attention should be given to electrolyte and acid-base balance in patients experiencing severe or prolonged diarrhea or patients receiving concomitant diuretic drugs.

Proarrhythmic events must be anticipated not only on initiating therapy, but with every upward dose adjustment [ see Dosage and Administration (2.1) ].

In general, do not use sotalol with other drugs known to cause QT prolongation [see Drug Interactions (7.1)].

5.2 Bradycardia/Heart Block/Sick Sinus Syndrome

Sinus bradycardia (heart rate less than 50 bpm) occurred in 13% of patients receiving sotalol in clinical trials, and led to discontinuation in about 3% of patients. Bradycardia itself increases the risk of Torsade de Pointes. Sinus pause, sinus arrest and sinus node dysfunction occur in less than 1% of patients. The incidence of 2nd- or 3rd-degree AV block is approximately 1%.

Sotalol Hydrochloride Tablets are contraindicated in patients with sick sinus syndrome because it may cause sinus bradycardia, sinus pauses or sinus arrest.

5.3 Hypotension

Sotalol produces significant reductions in both systolic and diastolic blood pressures and may result in hypotension. Monitor hemodynamics in patients with marginal cardiac compensation.

5.4 Heart Failure

New onset or worsening heart failure may occur during initiation or uptitration of sotalol because of its beta- blocking effects. Monitor for signs and symptoms of heart failure and discontinue treatment if symptoms occur.

5.5 Cardiac Ischemia after Abrupt Discontinuation

Following abrupt cessation of therapy with beta adrenergic blockers, exacerbations of angina pectoris and myocardial infarction may occur. When discontinuing chronically administered Sotalol Hydrochloride Tablets, particularly in patients with ischemic heart disease, gradually reduce the dosage over a period of 1–2 weeks, if possible, and monitor the patient. If angina markedly worsens or acute coronary ischemia develops, treat appropriately (consider use of an alternative beta blocker). Warn patients not to interrupt therapy without their physician’s advice. Because coronary artery disease may be common, but unrecognized, in patients treated with sotalol, abrupt discontinuation may unmask latent coronary insufficiency.

5.6 Bronchospasm

Patients with bronchospastic diseases (for example chronic bronchitis and emphysema) should not receive beta- blockers. If Sotalol Hydrochloride Tablets are to be administered, use the smallest effective dose, to minimize inhibition of bronchodilation produced by endogenous or exogenous catecholamine stimulation of beta 2 receptors.

5.7 Masked Signs of Hypoglycemia in Diabetics

Beta blockers may mask tachycardia occurring with hypoglycemia, but other manifestations such as dizziness and sweating may not be significantly affected. Elevated blood glucose levels and increased insulin requirements can occur in diabetic patients.

5.8 Thyroid Abnormalities

Avoid abrupt withdrawal of beta-blockade in patients with thyroid disease because it may lead to an exacerbation of symptoms of hyperthyroidism, including thyroid storm. Beta-blockade may mask certain clinical signs (for example, tachycardia) of hyperthyroidism.

5.9 Anaphylaxis

While taking beta-blockers, patients with a history of anaphylactic reaction to a variety of allergens may have a more severe reaction on repeated challenge, either accidental, diagnostic or therapeutic. Such patients may be unresponsive to the usual doses of epinephrine used to treat the allergic reaction.

5.10 Major Surgery

Chronically administered beta-blocking therapy should not be routinely withdrawn prior to major surgery; however, the impaired ability of the heart to respond to reflex adrenergic stimuli may augment the risks of general anesthesia and surgical procedures.

6 ADVERSE REACTIONS

6.1 Clinical Trials Experience

Because clinical trials are conducted under widely varying conditions, adverse reaction rates observed in the clinical trials of a drug cannot be directly compared to rates in the clinical trials of another drug and may not reflect the rates observed in practice.
Adverse reactions that are clearly related to sotalol are those which are typical of its Class II (beta-blocking) and Class III (cardiac action potential duration prolongation) effects and are dose related.
Ventricular Arrhythmias
Serious Adverse Reactions
In patients with a history of sustained ventricular tachycardia, the incidence of Torsade de Pointes during oral sotalol treatment was 4% and worsened VT was about 1%; in patients with other less serious ventricular arrhythmias the incidence of Torsade de Pointes was 1% and new or worsened VT was about 0.7%. Incidence of Torsade de Pointes arrhythmias in patients with VT/VF are shown in Table 3 below.

Table 3: Percent Incidence of Torsade de Pointes and Mean QTc Interval by Dose For Patients With Sustained VT/VF
Daily Dose (mg) | Torsade de Pointes Incidence | Mean QTc [highest on-therapy value] (msec)
80 | 0 (69) | 463 (17)
160 | 0.5 (832) | 467 (181)
320 | 1.6 (835) | 473 (344)
480 | 4.4 (459) | 483 (234)
640 | 3.7 (324) | 490 (185)
>640 | 5.8 (103) | 512 (62)
() Number of patients assessed

Table 4 below relates the incidence of Torsade de Pointes to on-therapy QTc and change in QTc from baseline in patients with ventricular arrhythmias. It should be noted, however, that the highest on-therapy QTc was in many cases the one obtained at the time of the Torsade de Pointes event, so that the table overstates the predictive value of a high QTc.

Table 4: Relationship Between QTc Interval Prolongations and Torsade de Pointes
On-Therapy QTc Interval (msec) | Incidence of Torsade de Pointes | Change from Baseline in QTc (msec) | Incidence of Torsade de Pointes
<500 | 1.3% (1787) | <65 | 1.6% (1516)
500-525 | 3.4% (236) | 65-80 | 3.2% (158)
525-550 | 5.6% (125) | 80-100 | 4.1% (146)
>550 | 10.8% (157) | 100-130 | 5.2% (115)
 |  | >130 | 7.1% (99)
() Number of patients assessed

Table 5: Incidence (%) of Common Adverse Reactions (2% in the Placebo group and less frequent than Sotalol Hydrochloride Tablets groups) in a Placebo-controlled Parallel-group Comparison Study of Patients with Ventricular Ectopy
Body System/Adverse Reaction (Preferred Term) | Placebo | Sotalol Hydrochloride Total Daily Dose
Body System/Adverse Reaction (Preferred Term) | N=37 (%) | 320 mg N=38 (%) | 640 mg N=39 (%)
CARDIOVASCULAR
Chest Pain | 5.4 | 7.9 | 15.4
Dyspnea | 2.7 | 18.4 | 20.5
Palpitation | 2.7 | 7.9 | 5.4
Vasodilation | 2.7 | 0.0 | 5.1
NERVOUS SYSTEM
Asthenia | 8.1 | 10.5 | 20.5
Dizziness | 5.4 | 13.2 | 17.9
Fatigue | 10.8 | 26.3 | 25.6
Headache | 5.4 | 5.3 | 7.7
Lightheaded | 8.1 | 15.8 | 5.1
Sleep Problem | 2.7 | 2.6 | 7.7
RESPIRATORY
Upper Respiratory Tract Problem | 2.7 | 2.6 | 12.8
SPECIAL SENSES
Visual Problem | 2.7 | 5.3 | 0.0

The most common adverse reactions leading to discontinuation of Sotalol Hydrochloride Tablets in trials of patients with ventricular arrhythmias are: fatigue 4%, bradycardia (less than 50 bpm) 3%, dyspnea 3%, proarrhythmia 3%, asthenia 2%, and dizziness 2%. Incidence of discontinuation for these adverse reactions was dose related.

One case of peripheral neuropathy that resolved on discontinuation of Sotalol Hydrochloride Tablets and recurred when the patient was rechallenged with the drug was reported in an early dose tolerance study.

Pediatric Patients

In an unblinded multicenter trial of 25 pediatric patients with SVT and/or VT receiving daily doses of 30, 90 and 210 mg/m^2 with dosing every 8 ours for a total of 9 doses, no Torsade de Pointes or other serious new arrhythmias were observed. One (1) patient, receiving 30 mg/m^2 daily, was discontinued because of increased frequency of sinus pauses/bradycardia. Additional cardiovascular AEs were seen at the 90 and 210 mg/m^2 daily dose levels. They included QT prolongation (2 patients), sinus pauses/bradycardia (1 patient), increased severity of atrial flutter and reported chest pain (1 patient). Values for QTc 525 msec were seen in 2 patients at the 210 mg/m^2 daily dose level. Serious adverse events including death, Torsade de Pointes, other proarrhythmias, high-degree A-V blocks, and bradycardia have been reported in infants and/or children.

7 DRUG INTERACTIONS

7.1 Antiarrhythmics and other QT Prolonging Drugs

Sotalol has not been studied with other drugs that prolong the QT interval such as antiarrhythmics, some phenothiazines, tricyclic antidepressants, certain oral macrolides and certain quinolone antibiotics. Discontinue Class I or Class III antiarrhythmic agents for at least three half-lives prior to dosing with sotalol. Class Ia antiarrhythmic drugs, such as disopyramide, quinidine and procainamide and other Class III drugs (for example, amiodarone) are not recommended as concomitant therapy with Sotalol Hydrochloride Tablets, because of their potential to prolong refractoriness [ see Warnings and Precautions (5.2) ]. There is only limited experience with the concomitant use of Class Ib or Ic antiarrhythmics. Additive Class II effects would also be anticipated with the use of other beta-blocking agents concomitantly with Sotalol Hydrochloride Tablets.

7.2 Digoxin

Proarrhythmic events were more common in sotalol treated patients also receiving digoxin; it is not clear whether this represents an interaction or is related to the presence of CHF, a known risk factor for proarrhythmia, in the patients receiving digoxin. Both digitalis glycosides and beta-blockers slow atrioventricular conduction and decrease heart rate. Concomitant use can increase the risk of bradycardia.

7.3 Calcium-Channel Blocking Drugs

Sotalol and calcium-blocking drugs can be expected to have additive effects on atrioventricular conduction or ventricular function. Monitor such patients for evidence of bradycardia and hypotension.

7.4 Catecholamine-Depleting Agents

Concomitant use of catecholamine-depleting drugs, such as reserpine and guanethidine, with a beta-blocker may produce an excessive reduction of resting sympathetic nervous tone. Monitor such patients for evidence of hypotension and/or marked bradycardia which may produce syncope.

7.5 Insulin and Oral Antidiabetics

Hyperglycemia may occur, and the dosage of insulin or antidiabetic drugs may require adjustment [ see Warnings and Precautions 5.7) ].

7.6 Clonidine

Concomitant use with sotalol increases the risk of bradycardia. Because beta-blockers may potentiate the rebound hypertension sometimes observed after clonidine discontinuation, withdraw sotalol several days before the gradual withdrawal of clonidine to reduce the risk of rebound hypertension.

7.7 Antacids

Avoid administration of oral sotalol within 2 hours of antacids containing aluminum oxide and magnesium hydroxide.

8 USE IN SPECIAL POPULATIONS

8.1 Pregnancy

Pregnancy Category B

There are no adequate and well-controlled studies in pregnant women. Sotalol has been shown to cross the placenta, and is found in amniotic fluid. In animal studies there was no increase in congenital anomalies, but an increase in early resorptions occurred at sotalol doses 18 times the maximum recommended human dose (MRHD, based on surface area). Animal reproductive studies are not always predictive of human response.

Reproduction studies in rats and rabbits during organogenesis at 9 and 7 times the MRHD (based on surface area), respectively, did not reveal any teratogenic potential associated with sotalol. In rabbits, a dose of sotalol 6 times the MRHD produced a slight increase in fetal death as well as maternal toxicity. This effect did not occur at sotalol dose 3 times the MRHD. In rats a sotalol dose 18 times the MRHD increased the number of early resorptions, while a dose 2.5 times the MRHD, produced no increase in early resorptions.

8.3 Nursing Mothers

Sotalol is excreted in the milk of laboratory animals and has been reported to be present in human milk. Discontinue nursing on Sotalol Hydrochloride Tablets.

8.4 Pediatric Use

The safety and effectiveness of sotalol in children have not been established. However, the Class III electrophysiologic and beta-blocking effects, the pharmacokinetics, and the relationship between the effects (QTc interval and resting heart rate) and drug concentrations have been evaluated in children aged between 3 days and 12 years old [see Dosage and Administration (2.4) and Clinical Pharmacology (12.2)].

8.6 Renal Impairment

Sotalol is mainly eliminated via the kidneys. Dosing intervals should be adjusted based on creatinine clearance [ see Dosage and Administration (2.5) ].

10 OVERDOSAGE

Intentional or accidental overdosage with sotalol has resulted in death.

Symptoms and Treatment of Overdosage

The most common signs to be expected are bradycardia, congestive heart failure, hypotension, bronchospasm and hypoglycemia. In cases of massive intentional overdosage (2–16 grams) of sotalol the following clinical findings were seen: hypotension, bradycardia, cardiac asystole, prolongation of QT interval, Torsade de Pointes, ventricular tachycardia, and premature ventricular complexes. If overdosage occurs, therapy with sotalol should be discontinued and the patient observed closely. Because of the lack of protein binding, hemodialysis is useful for reducing sotalol plasma concentrations. Patientsshould be carefully observed until QT intervals are normalized and the heart rate returns to levels >50 bpm.

The occurrence of hypotension following an overdose may be associated with an initial slow drug elimination phase (half-life of 30 hours) thought to be due to a temporary reduction of renal function caused by the hypotension. In addition, if required, the following therapeutic measures are suggested:

Bradycardia or Cardiac Asystole: Atropine, another anticholinergic drug, a beta-adrenergic agonist or transvenous cardiac pacing.
Heart Block: (second and third degree) transvenous cardiac pacemaker.
Hypotension: (depending on associated factors) epinephrine rather than isoproterenol or norepinephrine may be useful.
Bronchospasm: Aminophylline or aerosol beta-2-receptor stimulant. Higher than normal doses of beta-2 receptor stimulants may be required.
Torsade de Pointes: DC cardioversion, transvenous cardiac pacing, epinephrine, magnesium sulfate.

11 DESCRIPTION

Sotalol Hydrochloride Tablets, USP contain sotalol hydrochloride, an antiarrhythmic drug with Class II (beta adrenoreceptor blocking) and Class III (cardiac action potential duration prolongation) properties. Sotalol Hydrochloride Tablets, USP are supplied as a light-blue, capsule-shaped tablet for oral administration. Sotalol hydrochloride is a white, crystalline solid with a molecular weight of 308.8. It is hydrophilic, soluble in water, propylene glycol and ethanol, but is only slightly soluble in chloroform. Chemically, sotalol hydrochloride is d,l-N-[4-[1-hydroxy-2-[(1-methylethyl) amino]ethyl]phenyl]methane-sulfonamide monohydrochloride. The molecular formula is C12H20N2O3 S∙HCl and is represented by the following structural formula:

Sotalol Hydrochloride Tablets, USP contain the following inactive ingredients: lactose monohydrate, microcrystalline cellulose, pregelatinized starch, FD&C Blue #2, colloidal silicon dioxide, stearic acid, magnesium stearate.

12 CLINCAL PHARMACOLOGY

12.1 Mechanism of Action

Sotalol has both beta-adrenoreceptor blocking (Vaughan Williams Class II) and cardiac action potential duration prolongation (Vaughan Williams Class III) antiarrhythmic properties. The two isomers of sotalol have similar Class III antiarrhythmic effects, while the l-isomer is responsible for virtually all of the beta-blocking activity. The beta-blocking effect of sotalol is non-cardioselective, half maximal at about 80 mg/day and maximal at doses between 320 and 640 mg/day. Sotalol does not have partial agonist or membrane stabilizing activity. Although significant beta-blockade occurs at oral doses as low as 25 mg, significant Class III effects are seen only at daily doses of 160 mg and above.

In children, a Class III electrophysiologic effect can be seen at daily doses of 210 mg/m^2 body surface area (BSA). A reduction of the resting heart rate due to the beta-blocking effect of sotalol is observed at daily doses ≥ 90 mg/m^2 in children.

12.2 Pharmacodynamics

Cardiac Electrophysiological Effects

Sotalol hydrochloride prolongs the plateau phase of the cardiac action potential in the isolated myocyte, as well as in isolated tissue preparations of ventricular or atrial muscle (Class III activity). In intact animals it slows heart rate, decreases AV nodal conduction and increases the refractory periods of atrial and ventricular muscle and conduction tissue.

In man, the Class II (beta-blockade) electrophysiological effects of sotalol are manifested by increased sinus cycle length (slowed heart rate), decreased AV nodal conduction and increased AV nodal refractoriness. The Class III electrophysiological effects in man include prolongation of the atrial and ventricular monophasic action potentials, and effective refractory period prolongation of atrial muscle, ventricular muscle, and atrio ventricular accessory pathways (where present) in both the anterograde and retrograde directions. With oral doses of 160 to 640 mg/day, the surface ECG shows dose-related mean increases of 40–100 msec in QT and 10–40 msec in QTc [ See Warnings and Precautions (5.1) ]. No significant alteration in QRS interval is observed.

In a small study (n=25) of patients with implanted defibrillators treated concurrently with Sotalol Hydrochloride Tablets, the average defibrillatory threshold was 6 joules (range 2–15 joules) compared to a mean of 16 joules for a nonrandomized comparative group primarily receiving amiodarone.

Twenty-five children in an unblinded, multicenter trial with SVT and/or ventricular tachyarrhythmias, aged between 3 days and 12 years (mostly neonates and infants), received an ascending titration regimen with daily doses of 30, 90 and 210 mg/m^2 with dosing every 8 hours for a total 9 doses. During steady-state, the respective average increases above baseline of the QTc interval were 2, 14, and 29 msec at the 3 dose levels. The respective mean maximum increases above baseline of the QTc interval were 23, 36, and 55 msec at the 3 dose levels. The steady-state percent increases in the RR interval were 3, 9 and 12%. The smallest children (BSA<0.33 m^2) showed a tendency for larger Class III effects (ΔQTc) and an increased frequency of prolongations of the QTc interval as compared with larger children (BSA ≥0.33 m^2). The beta-blocking effects also tended to be greater in the smaller children (BSA <0.33 m^2). Both the Class III and beta-blocking effects of sotalol were linearly related to the plasma concentrations.

Hemodynamics

In a study of systemic hemodynamic function measured invasively in 12 patients with a mean LV ejection fraction of 37% and ventricular tachycardia (9 sustained and 3 non-sustained), a median dose of 160 mg twice daily of Sotalol Hydrochloride Tablets produced a 28% reduction in heart rate and a 24% decrease in cardiac index at 2 hours post- dosing at steady-state. Concurrently, systemic vascular resistance and stroke volume showed nonsignificant increases of 25% and 8%, respectively. One patient was discontinued because of worsening congestive heart failure. Pulmonary capillary wedge pressure increased significantly from 6.4 mmHg to 11.8 mmHg in the 11 patients who completed the study. Mean arterial pressure, mean pulmonary artery pressure and stroke work index did not significantly change. Exercise and isoproterenol induced tachycardia are antagonized by Sotalol Hydrochloride Tablets, and total peripheral resistance increases by a small amount.

In hypertensive patients, sotalol produces significant reductions in both systolic and diastolic blood pressures. Although sotalol is usually well-tolerated hemodynamically, deterioration in cardiac performance may occur in patients with marginal cardiac compensation [ see Warnings and Precautions (5.3) ].

12.3 Pharmacokinetics

The pharmacokinetics of the d and l enantiomers of sotalol are essentially identical.

Absorption

In healthy subjects, the oral bioavailability of sotalol is 90–100%. After oral administration, peak plasma concentrations are reached in 2.5 to 4 hours, and steady-state plasma concentrations are attained within 2–3 days (that is, after 5–6 doses when administered twice daily). Over the dosage range 160–640 mg/day sotalol displays dose proportionality with respect to plasma concentrations. When administered with a standard meal, the absorption of sotalol was reduced by approximately 20% compared to administration in fasting state.

Distribution

Sotalol does not bind to plasma proteins. Distribution occurs to a central (plasma) and to a peripheral compartment. Sotalol crosses the blood brain barrier poorly.

Metabolism

Sotalol is not metabolized and is not expected to inhibit or induce any CYP450 enzymes.

Excretion

Excretion of sotalol is predominantly via the kidney in the unchanged form, and therefore lower doses are necessary in conditions of renal impairment [ see Dosage and Administration (2.5) ]. The mean elimination half- life of sotalol is 12 hours. Dosing every 12 hours results in trough plasma concentrations which are approximately one-half of those at peak.

Specific Populations

Pediatric: The combined analysis of a single-dose study and a multiple-dose study with 59 children, aged between 3 days and 12 years, showed the pharmacokinetics of sotalol to be first order. A daily dose of 30 mg/m^2 of sotalol was administered in the single dose study and daily doses of 30, 90 and 210 mg/m^2 were administered every 8 hours in the multi-dose study. After rapid absorption with peak levels occurring on average between 2–3 hours following administration, sotalol was eliminated with a mean half-life of 9.5 hours.

Steady-state was reached after 1–2 days. The average peak to trough concentration ratio was 2. BSA was the most important covariate and more relevant than age for the pharmacokinetics of sotalol. The smallest children (BSA<0.33m^2) exhibited a greater drug exposure (+59%) than the larger children who showed a uniform drug concentration profile. The intersubject variation for oral clearance was 22%.

Geriatric: Age does not significantly alter the pharmacokinetics of Sotalol Hydrochloride Tablets, but impaired renal function in geriatric patients can increase the terminal elimination half-life, resulting in increased drug accumulation.

Renal Impairment: Sotalol is mainly eliminated via the kidneys through glomerular filtration and to a small degree by tubular secretion. There is a direct relationship between renal function, as measured by serum creatinine or creatinine clearance, and the elimination rate of sotalol. The half-life of sotalol is prolonged (up to 69 hours) in anuric patients. Doses or dosing intervals should be adjusted based on creatinine clearance [ see Dosage and Administration (2.5) ].

Hepatic Impairment: Patients with hepatic impairment show no alteration in clearance of sotalol.

Drug-Drug Interactions:

Antacids: Administration of oral sotalol within 2 hours of antacids may result in a reduction in Cmax and AUC of 26% and 20%, respectively, and consequently in a 25% reduction in the bradycardic effect at rest.
Administration of the antacid two hours after oral sotalol has no effect on the pharmacokinetics or pharmacodynamics of sotalol.

No pharmacokinetic interactions were observed with hydrochlorothiazide or warfarin.

13 NONCLINICAL TOXICOLOGY

13.1 Carcinogenesis, Mutagenesis, Impairment of Fertility

No evidence of carcinogenic potential was observed in rats during a 24-month study at 137–275 mg/kg/day (approximately 30 times the maximum recommended human oral dose (MRHD) as mg/kg or 5 times the MRHD as mg/m^2) or in mice, during a 24-month study at 4141–7122 mg/kg/day (approximately 450–750 times the MRHD as mg/kg or 36–63 times the MRHD as mg/m^2).

Sotalol has not been evaluated in any specific assay of mutagenicity or clastogenicity.

No significant reduction in fertility occurred in rats at oral doses of 1000 mg/kg/day (approximately 100 times the MRHD as mg/kg or 18 times the MRHD as mg/m2) prior to mating, except for a small reduction in the number of offspring per litter.

Reproduction studies in rats and rabbits during organogenesis at 100 and 22 times the MRHD as mg/kg (9 and 7 times the MRHD as mg/m^2), respectively, did not reveal any teratogenic potential associated with sotalol HCl. In rabbits, a high dose of sotalol HCl (160 mg/kg/day) at 16 times the MRHD as mg/kg (6 times the MRHD as mg/m^2) produced a slight increase in fetal death, and maternal toxicity. Eight times the maximum dose (80 mg/kg/day or 3 times the MRHD as mg/m^2) did not result in an increased incidence of fetal deaths. In rats, 1000 mg/kg/day sotalol HCl, 100 times the MRHD (18 times the MRHD as mg/m^2), increased the number of early resorptions, while at 14 times the maximum dose (2.5 times the MRHD as mg/m^2), no increase in early resorptions was noted. However, animal reproduction studies are not always predictive of human response.

14 CLINICAL STUDIES

14.1 Ventricular Arrhythmias

Sotalol Hydrochloride Tablets have been studied in life-threatening and less severe arrhythmias. In patients with frequent premature ventricular complexes (VPC), Sotalol Hydrochloride Tablets were significantly superior to placebo in reducing VPCs, paired VPCs and non-sustained ventricular tachycardia (NSVT); the response was dose-related through 640 mg/day with 80–85% of patients having at least a 75% reduction of VPCs. Sotalol Hydrochloride Tablets were also superior, at the doses evaluated, to propranolol (40–80 mg TID) and similar to quinidine (200–400 mg QID) in reducing VPCs. In patients with life-threatening arrhythmias [sustained ventricular tachycardia/fibrillation (VT/VF)], Sotalol Hydrochloride Tablets were studied acutely [by suppression of programmed electrical stimulation (PES) induced VT and by suppression of Holter monitor evidence of sustained VT] and, in acute responders, chronically.

In a double-blind, randomized comparison of Sotalol Hydrochloride Tablets and procainamide given intravenously (total of 2 mg/kg Sotalol Hydrochloride vs. 19 mg/kg of procainamide over 90 minutes), Sotalol Hydrochloride Tablets suppressed PES induction in 30% of patients vs. 20% for procainamide (p=0.2).

In a randomized clinical trial [Electrophysiologic Study Versus Electrocardiographic Monitoring (ESVEM) Trial] comparing choice of antiarrhythmic therapy by PES suppression vs. Holter monitor selection (in each case followed by treadmill exercise testing) in patients with a history of sustained VT/VF who were also inducible by PES, the effectiveness acutely and chronically of Sotalol Hydrochloride Tablets was compared with that of 6 other drugs (procainamide, quinidine, mexiletine, propafenone, imipramine and pirmenol). Overall response, limited to first randomized drug, was 39% for Sotalol Hydrochloride Tablets and 30% for the pooled other drugs. Acute response rate for first drug randomized using suppression of PES induction was 36% for Sotalol Hydrochloride Tablets vs. a mean of 13% for the other drugs. Using the Holter monitoring endpoint (complete suppression of sustained VT, 90% suppression of NSVT, 80% suppression of VPC pairs, and at least 70% suppression of VPCs), Sotalol Hydrochloride Tablets yielded 41% response vs. 45% for the other drugs combined. Among responders placed on long-term therapy identified acutely as effective (by either PES or Holter), Sotalol Hydrochloride Tablets, when compared to the pool of other drugs, had the lowest two- year mortality (13% vs. 22%), the lowest two-year VT recurrence rate (30% vs. 60%), and the lowest withdrawal rate (38% vs. about 75–80%). The most commonly used doses of Sotalol Hydrochloride Tablets in this trial were 320– 480 mg/day (66% of patients), with 16% receiving 240 mg/day or less and 18% receiving 640 mg or more.

It cannot be determined, however, in the absence of a controlled comparison of Sotalol Hydrochloride Tablets vs. no pharmacologic treatment (for example, in patients with implanted defibrillators) whether Sotalol Hydrochloride Tablets response causes improved survival or identifies a population with a good prognosis.

Sotalol Hydrochloride Tablets have not been shown to enhance survival in patients with ventricular arrhythmias.

14.3 Clinical Studies in Patients with Myocardial Infarction

In a large double-blind, placebo controlled secondary prevention (postinfarction) trial (n=1,456); Sotalol Hydrochloride Tablets were given as a non-titrated initial dose of 320 mg once daily. Sotalol Hydrochloride Tablets did not produce a significant increase in survival (7.3% mortality on Sotalol Hydrochloride Tablets vs. 8.9% on placebo, p=0.3), but overall did not suggest an adverse effect on survival. There was, however, a suggestion of an early (i.e., first 10 days) excess mortality (3% on Sotalol Hydrochloride Tablets vs. 2% on placebo).

In a second small trial (n=17 randomized to Sotalol Hydrochloride Tablets) where Sotalol Hydrochloride Tablets was administered at high doses (for example, 320 mg twice daily) to high-risk post-infarction patients (ejection fraction <40% and either >10 VPC/hr or VT on Holter), there were 4 fatalities and 3 serious hemodynamic/electrical adverse events within two weeks of initiating Sotalol Hydrochloride Tablets.

16 HOW SUPPLIED/STORAGE AND HANDLING

Sotalol Hydrochloride Tablets, USP; capsule-shaped light-blue scored tablets, imprinted with the strength and "B106"

NDC: 72162-2523-1: 100 Tablets in a BOTTLE

Store at 25°C (77°F); excursions permitted to 15-30°C (59-86°F) [See USP Controlled Room Temperature].

Repackaged/Relabeled by:
Bryant Ranch Prepack, Inc.
Burbank, CA 91504

17 PATIENT COUNSELING INFORMATION

- Advise patients to contact their health care provider in the event of syncope, pre-syncopal symptoms or cardiac palpitations.
- Advise patients that their electrolytes and ECG will be monitored during treatment [ see Warnings and Precautions (5.1) ].
- Advise patients to contact their healthcare provider in the event of conditions that could lead to electrolyte changes such as severe diarrhea, unusual sweating, vomiting, less appetite than normal or excessive thirst [see Warnings and Precautions (5.1)].
- Advise patients not to change the Sotalol Hydrochloride Tablets dose prescribed by their healthcare provider.
- Advise patients that they should not miss a dose, but if they do miss a dose they should not double the next dose to compensate for the missed dose: they should take the next dose at the regularly scheduled time [ see Dosage and Administration (2) ].
- Advise patients to not interrupt or discontinue Sotalol Hydrochloride Tablets without their physician’s advice, that they should get their prescription for sotalol filled and refilled on time so they do not interrupt treatment [ see Dosage and Administration (2) ].
- Advise patients to not start taking other medications without first discussing new medications with their healthcare provider.
- Advice patients that they should avoid taking Sotalol Hydrochloride Tablets within two hours of taking antacids that contain aluminum oxide or magnesium hydroxide [ see Drug Interactions (7.7) ].

Manufactured for
Beximco Pharmaceuticals USA Inc.
Suwanee, GA 30024, USA

Manufactured by
BEXIMCO PHARMACEUTICALS LTD.
126, Kathaldia, Tongi, Gazipur, 1711, Bangladesh

Distributed by:
Bayshore Pharmaceuticals LLC
Short Hills, NJ 07078

5001246 230117

PACKAGE LABEL

Sotalol Hydrochloride 160 mg Tablets #100